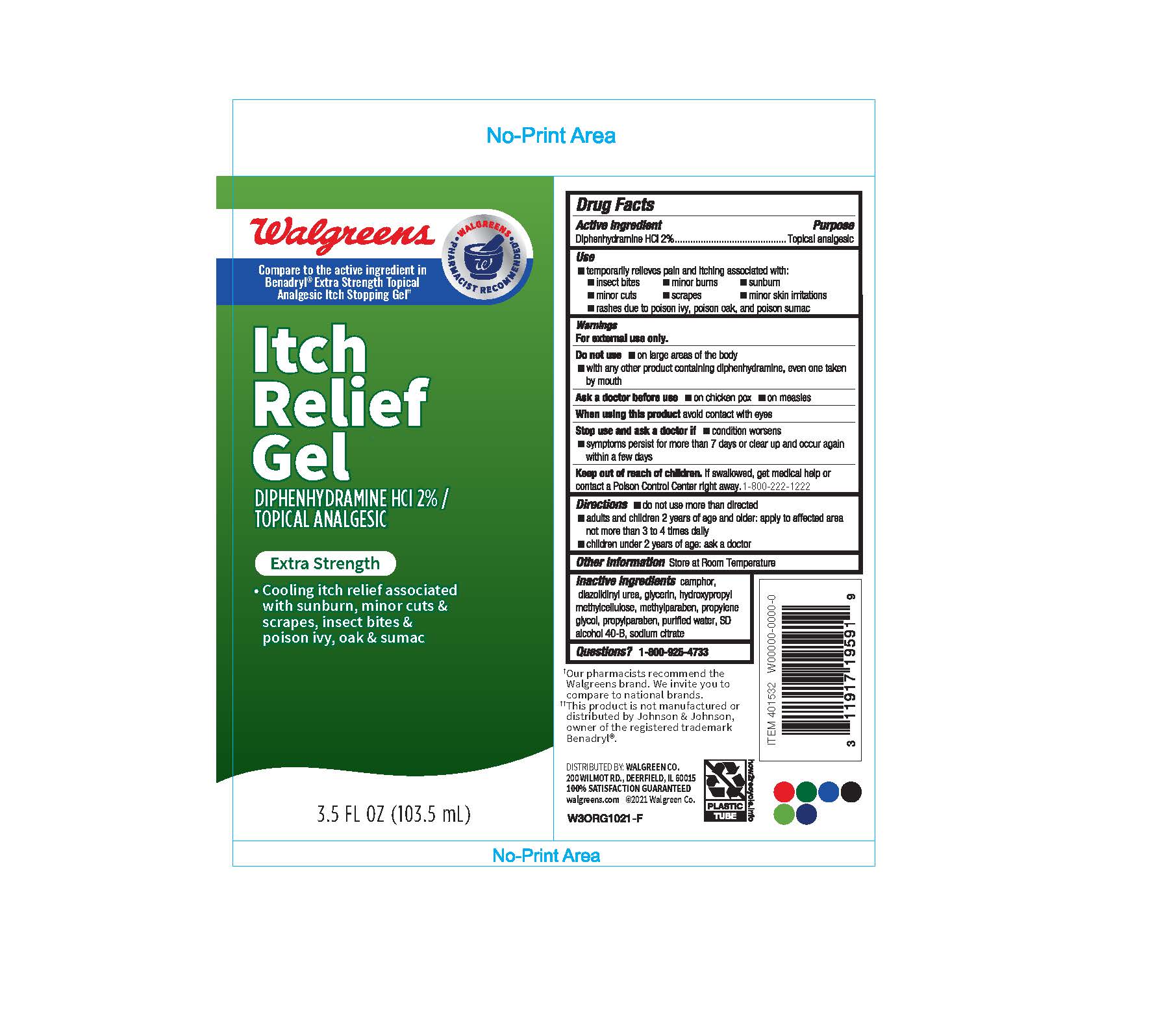 DRUG LABEL: Walgreen Itch Relief Gel
NDC: 0363-0354 | Form: GEL
Manufacturer: Walgreens
Category: otc | Type: HUMAN OTC DRUG LABEL
Date: 20260115

ACTIVE INGREDIENTS: DIPHENHYDRAMINE HYDROCHLORIDE 20 mg/1 mL
INACTIVE INGREDIENTS: ALCOHOL; CAMPHOR (SYNTHETIC); CITRIC ACID MONOHYDRATE; DIAZOLIDINYL UREA; GLYCERIN; HYPROMELLOSE, UNSPECIFIED; METHYLPARABEN; PROPYLENE GLYCOL; PROPYLPARABEN; WATER; SODIUM CITRATE, UNSPECIFIED FORM

Walgreens® ITCH RELIEF GEL

Drug Facts

Active ingredient

Diphenhydramine HCl 2%

Purpose

Topical Analgesic

Use

- temporarily relieves pain and itching associated with:
  - insect bites
  - minor burns
  - sunburn
  - minor cuts
  - scrapes
  - minor skin irritations
  - rashes due to poison ivy, poison oak, and poison sumac

Warnings

For external use only.

Do not use

- on large areas of the body
- with any other product containing diphenhydramine, even one taken by mouth

Ask a doctor before use

- on chicken pox
- on measles

When using this productavoid contact with eyes

Stop use and ask a doctor if

- condition worsens
- symptoms persist for more than 7 days or clear up and occur again within a few days

Keep out of reach of children.If swallowed, get medical help or contact a Poison Control Center right away.

Directions

- do not use more than directed
- adults and children 2 years of age and older: apply to affected area not more than 3 to 4 times daily
- children under 2 years of age: ask a doctor

Other information

Store at Room Temperature

Inactive ingredients

SD alcohol 38-B, camphor, citric acid, diazolidinyl urea, glycerin, hydroxypropyl methylcellulose, methylparaben, propylene glycol, propylparaben, purified water, sodium citrate